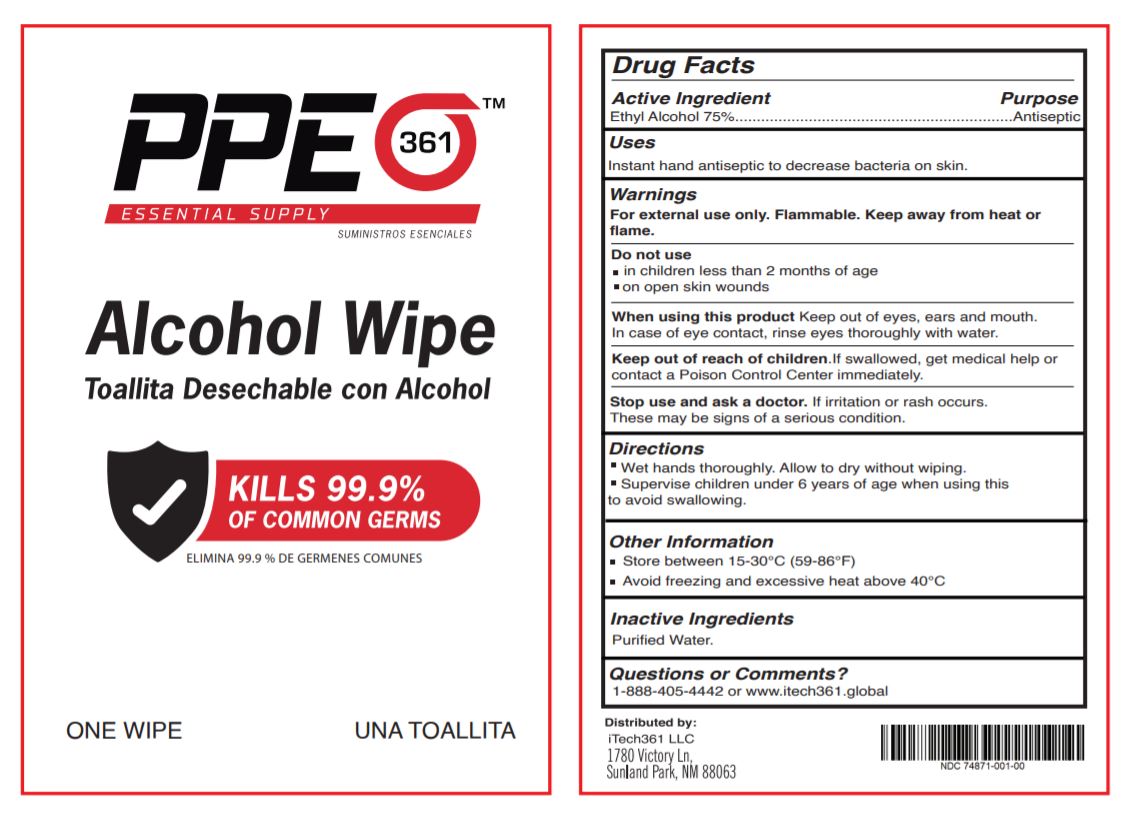 DRUG LABEL: PPE361 ALCOHOL WIPE 1
NDC: 74871-001 | Form: CLOTH
Manufacturer: ITECH 361 LLC
Category: otc | Type: HUMAN OTC DRUG LABEL
Date: 20210108

ACTIVE INGREDIENTS: ALCOHOL 75 mL/100 mL
INACTIVE INGREDIENTS: WATER

ITECH361 PPE361 ALCOHOL WIPE 1

ACTIVE INGREDIENT

Ethyl Alcohol 75%

PURPOSE

Antiseptic

USES

Instant hand antiseptic to decrease bacteria on skin.

WARNINGS

For external use only. Flammable. Keep away from heat or flame

Do not use

■ in children less than 2 months of age

■ on open skin wounds

When using this product keep out of eyes, ears, and mouth. In case of contact with eyes, rinse eyes thoroughly with water.

Stop use and ask a doctor if irritation or rash occurs. These may be signs of a serious condition.

Keep out of reach of children. If swallowed, get medical help or contact a Poison Control Center right away.

Keep out of reach of children If swallowed get medical help or contact a Poison Control Center right away.

DIRECTIONS

■ Wet hands thoroughly. Allow to dry without wiping.

■ Supervise children under 6 years of age when using this product to avoid swallowing.

OTHER INFORMATION

■ Store between 15-30°C (59-86°F)

■ Avoid freezing and excessive heat above 40°C (104°F)

INACTIVE INGREDIENTS

Water (Aqua).

QUESTIONS OR COMMENTS?

1-888-405-4442 or visit www.itech361.global